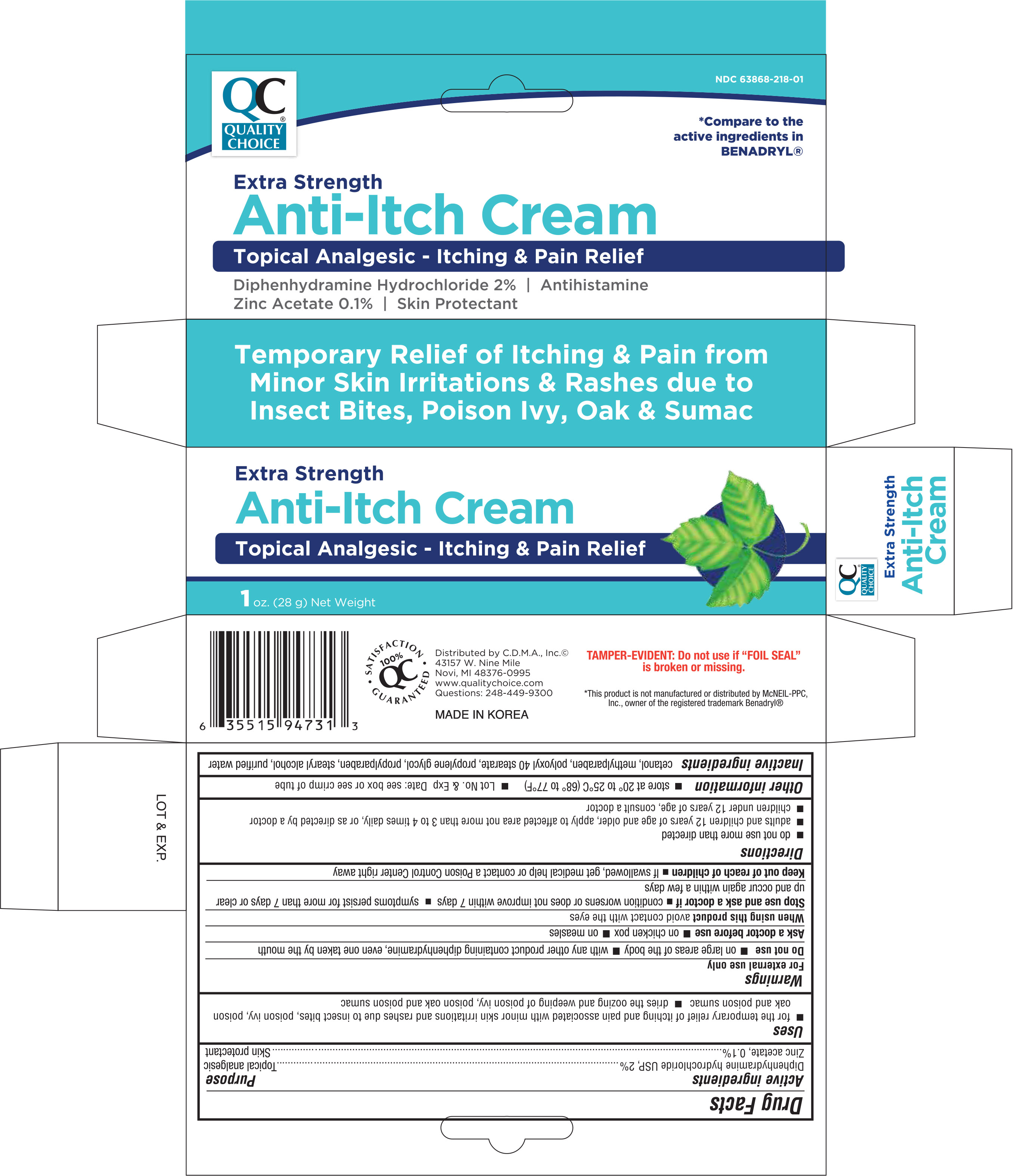 DRUG LABEL: Anti itch Topical Analgesic
NDC: 63868-218 | Form: CREAM
Manufacturer: Chain Drug Marketing Associations Inc
Category: otc | Type: HUMAN OTC DRUG LABEL
Date: 20191219

ACTIVE INGREDIENTS: DIPHENHYDRAMINE HYDROCHLORIDE 2 g/100 g; ZINC ACETATE 0.1 g/100 g
INACTIVE INGREDIENTS: CETYL ALCOHOL; METHYLPARABEN; POLYOXYL 40 STEARATE; PROPYLENE GLYCOL; PROPYLPARABEN; STEARYL ALCOHOL; WATER

Quality Choice Extra Strength Itch Stopping Cream 1 oz. 94731 TG/CMI 2019

Active Ingredients Purpose

Diphenhydramine HCI 2%........................................................Topical analgesic

Zinc acetate, 0.1%.................................................................... Skin protectant

Uses

- temporarily relieves pain and itching associated with:
- insect bites
- minor burns
- minor skin irritations
- sunburn
- minor cuts
- scrapes
- rashes due to poison ivy, oak, and sumac
- dries the oozing and weeping of poison:
- ivy oak
- sumac

Warnings

For external use only

Do not use

- with any other product containing diphenhydramine, even one taken by mouth
- on large areas of the body

Ask a doctor before use

- on chicken pox
- on measles

When using this product avoid contact with the eyes

Stop use and ask a doctor if

- condition worsens or does not improve within 7 days
- symptoms persist for more than 7 days or clear up and occur again within a few days

PREGNANCY OR BREAST FEEDING

If pregnant or breast-feeding, ask a health professional before use.

Keep out of reach of children

If swallowed, get medical help or contact a Poison Control Center right away

Directions

- do not use more than directed
- adults and children 12 years of age and older: apply to affected area not more than 3 to 4 times daily
- children under 12 years of age: consult a doctor

Other information

- store at 20° to 25°C (68° to 77°F)

inactive ingredients

cetyl alcohol, methylparaben, polyoxyl 40 stearate, propylene glycol, propylparaben, purified water, stearyl alcohol

DOSAGE AND ADMINISTRATION

DISTRIBUTED BY:

C.D.M.A. INC.

43157 W. NINE MILE

NOVA, MI 48376-0995

Made in Korea